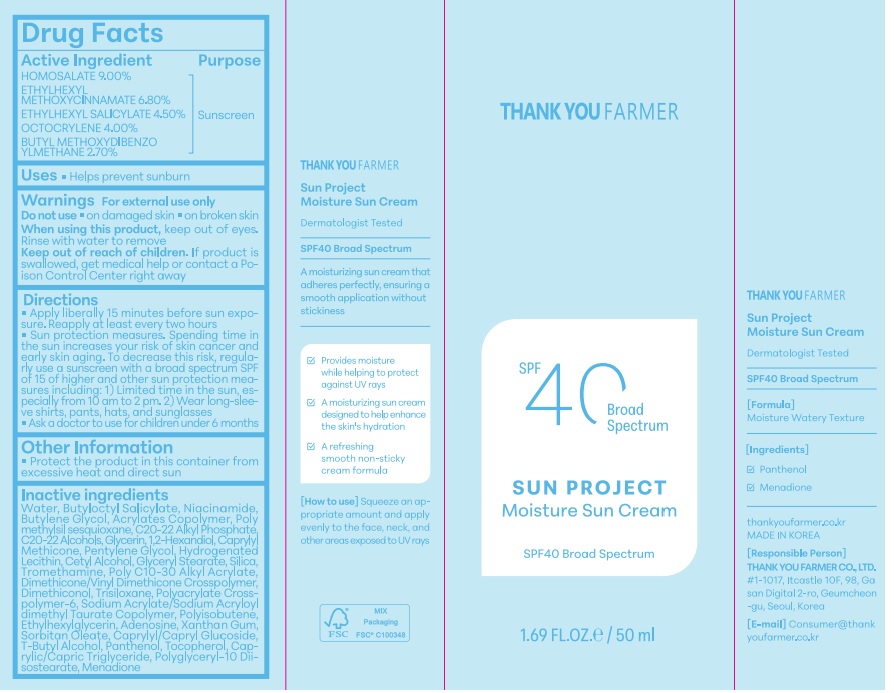 DRUG LABEL: Sun Project Moisture
NDC: 70618-040 | Form: CREAM
Manufacturer: THANK YOU FARMER CO., LTD
Category: otc | Type: HUMAN OTC DRUG LABEL
Date: 20260113

ACTIVE INGREDIENTS: OCTISALATE 2.25 g/50 mL; OCTINOXATE 3.4 g/50 mL; OCTOCRYLENE 2 g/50 mL; AVOBENZONE 1.35 g/50 mL; HOMOSALATE 4.5 g/50 mL
INACTIVE INGREDIENTS: BUTYLOCTYL SALICYLATE; BUTYL ACRYLATE/METHYL METHACRYLATE/METHACRYLIC ACID COPOLYMER (18000 MW); WATER; BUTYLENE GLYCOL; GLYCERIN; PENTYLENE GLYCOL; 1,2-HEXANEDIOL; POLYMETHYLSILSESQUIOXANE (4.5 MICRONS); C20-22 ALCOHOLS; CETYL ALCOHOL; DIMETHICONOL (100000 CST); TRISILOXANE; AMMONIUM ACRYLOYLDIMETHYLTAURATE; HYDROGENATED POLYISOBUTENE (1300 MW); ADENOSINE; TOCOPHEROL; TROMETHAMINE; GLYCERYL STEARATE SE; NIACINAMIDE; HYDROGENATED SOYBEAN LECITHIN; CAPRYLYL/CAPRYL OLIGOGLUCOSIDE; TERT-BUTYL ALCOHOL; MENADIONE; SILICON DIOXIDE; SODIUM ACRYLATE/SODIUM ACRYLOYLDIMETHYLTAURATE COPOLYMER (4000000 MW); XANTHAN GUM; C20-22 ALKYL PHOSPHATE; CAPRYLYL TRISILOXANE; DIMETHICONE/VINYL DIMETHICONE CROSSPOLYMER (SOFT PARTICLE); SORBITAN OLEATE DECYLGLUCOSIDE CROSSPOLYMER; MEDIUM-CHAIN TRIGLYCERIDES; POLYGLYCERYL-10 ISOSTEARATE; ETHYLHEXYLGLYCERIN; PANTHENOL; BEHENYL ACRYLATE POLYMER

Active Ingredient

Active Ingredient:HOMOSALATE 9%, ETHYLHEXYL METHOXYCINNAMATE 6.8%, ETHYLHEXYL SALICYLATE 4.5%, OCTOCRYLENE 4%, BUTYL METHOXYDIBENZOYLMETHANE 2.7%

Purpose

Purpose-Sunscreen, Uses-Helps prevent sunburn

When using

When using this product, keep out of eyes. Rinse with water to remove

Keep Out Of Reach of Children- If product is swallowed, get medical help or contact a Poison Control Center right away

Ask a doctor to use for children under 6 months

Do not use on damaged skin, on broken skin

Warning

Warning-For external use only

Inactive Ingredients

WATER, BUTYLOCTYL SALICYLATE, POLYMETHYLSILSESQUIOXANE, NIACINAMIDE, BUTYLENE GLYCOL, ACRYLATES COPOLYMER, C20-22 ALKYL PHOSPHATE, C20-22 ALCOHOLS, GLYCERIN, 1,2-HEXANEDIOL, CAPRYLYL METHICONE, PENTYLENE GLYCOL,CETYL ALCOHOL, POLY C10-30 ALKYL ACRYLATE, TROMETHAMINE, GLYCERYL STEARATE, SILICA, DIMETHICONE/VINYL DIMETHICONE CROSSPOLYMER, DIMETHICONOL, TRISILOXANE, POLYACRYLATE CROSSPOLYMER-6, SODIUM ACRYLATE/SODIUM ACRYLOYLDIMETHYL TAURATE COPOLYMER,POLYISOBUTENE, ETHYLHEXYLGLYCERIN, ADENOSINE, XANTHAN GUM, CAPRYLYL/CAPRYL GLUCOSIDE, SORBITAN OLEATE, T-BUTYL ALCOHOL, PANTHENOL, TOCOPHEROL, CAPRYLIC/CAPRIC TRIGLYCERIDE, POLYGLYCERYL-10 DIISOSTEARATE, HYDROGENATED LECITHIN
,MENADIONE

Other Safety Information-Protect the product in this container from excessive heat and direct sun

Incations & usage

Incations & usage-Helps prevent sunburn

Dosage & administration

Dosage & administration -Apply liberally 15 minutes before sun exposure. Reapply at least every two hours

PACKAGE LABEL

Package Label Principal Display Panel-Thank you Farmer, SPF40 Broad Spectrum, Sun Project Moisture Sun Creaml Sinscren, SPF40 Broad Spectrum, 1.69 FL.OZ/50ml